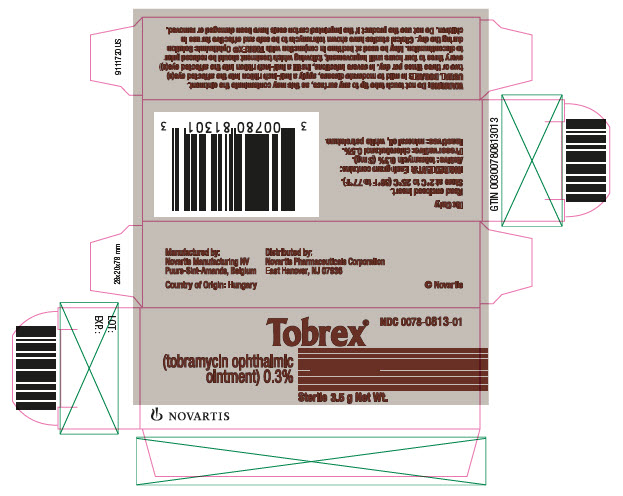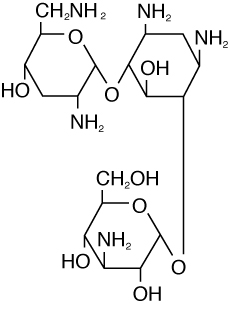 DRUG LABEL: TOBREX
NDC: 0078-0813 | Form: OINTMENT
Manufacturer: Novartis Pharmaceuticals Corporation
Category: prescription | Type: HUMAN PRESCRIPTION DRUG LABEL
Date: 20251216

ACTIVE INGREDIENTS: TOBRAMYCIN 3 mg/1 g
INACTIVE INGREDIENTS: CHLOROBUTANOL; MINERAL OIL; PETROLATUM

TOBREX® (tobramycin ophthalmic ointment) 0.3%

DESCRIPTION

TOBREX® (tobramycin ophthalmic ointment) 0.3% is a sterile topical ophthalmic antibiotic formulation prepared specifically for topical therapy of external ophthalmic infections.

Each gram of TOBREX (tobramycin ophthalmic ointment) 0.3% contains: Active: tobramycin 0.3% (3 mg). Preservative: chlorobutanol 0.5%. Inactives: mineral oil, white petrolatum.

Tobramycin is a water-soluble aminoglycoside antibiotic active against a wide variety of gram-negative and gram-positive ophthalmic pathogens.

The chemical structure of tobramycin is:

Molecular Formula:

C18H37N5O9

Molecular Weight: 467.52 g/mol

Chemical Name:

0-{3-amino-3-deoxy-α-D-gluco-pyranosyl-(1→4) }-0-{2,6-diamino-2,3,6-trideoxy-α-D-ribohexo-pyranosyl-(1→6) }-2-deoxystreptamine.

CLINICAL PHARMACOLOGY

In Vitro Data: In vitro studies have demonstrated tobramycin is active against susceptible strains of the following microorganisms: Staphylococci, including S. aureus and S. epidermidis (coagulase-positive and coagulase-negative), including penicillin-resistant strains.

Streptococci, including some of the Group A-beta-hemolytic species, some nonhemolytic species, and some Streptococcus pneumoniae.

Pseudomonas aeruginosa, Escherichia coli, Klebsiella pneumoniae, Enterobacter aerogenes, Proteus mirabilis, Morganella morganii, most Proteus vulgaris strains, Haemophilus influenzae and H. aegyptius, Moraxella lacunata, Acinetobacter calcoaceticus and some Neisseria species. Bacterial susceptibility studies demonstrate that in some cases, microorganisms resistant to gentamicin retain susceptibility to tobramycin.

INDICATIONS AND USAGE

TOBREX® (tobramycin ophthalmic ointment) 0.3 % is a topical antibiotic indicated in the treatment of external infections of the eye and its adnexa caused by susceptible bacteria. Appropriate monitoring of bacterial response to topical antibiotic therapy should accompany the use of TOBREX (tobramycin ophthalmic ointment) 0.3%. Clinical studies have shown tobramycin to be safe and effective for use in children.

CONTRAINDICATIONS

TOBREX (tobramycin ophthalmic ointment) 0.3 % is contraindicated in patients with known hypersensitivity to any of its components.

WARNINGS

NOT FOR INJECTION INTO THE EYE. Sensitivity to topically applied aminoglycosides may occur in some patients. Severity of hypersensitivity reactions may vary from local effects to generalized reactions such as erythema, itching, urticaria, skin rash, anaphylaxis, anaphylactoid reactions, or bullous reactions. If a sensitivity reaction to TOBREX (tobramycin ophthalmic ointment) 0.3% occurs, discontinue use.

PRECAUTIONS

General: As with other antibiotic preparations, prolonged use may result in overgrowth of nonsusceptible organisms, including fungi. If superinfection occurs, appropriate therapy should be initiated. Ophthalmic ointments may retard corneal wound healing.

Cross-sensitivity to other aminoglycoside antibiotics may occur; if hypersensitivity develops with this product, discontinue use and institute appropriate therapy.

Patients should be advised not to wear contact lenses if they have signs and symptoms of ocular infections.

PATIENT COUNSELING INFORMATION

Information for Patients: Do not touch tube tip to any surface, as this may contaminate the ointment.

Do not use the product if the imprinted carton seals have been damaged, or removed.

PREGNANCY

Pregnancy: Reproduction studies in three types of animals at doses up to thirty-three times the normal human systemic dose have revealed no evidence of impaired fertility or harm to the fetus due to tobramycin. There are, however, no adequate and well-controlled studies in pregnant women. Because animal studies are not always predictive of human response, this drug should be used during pregnancy only if clearly needed.

NURSING MOTHERS

Nursing Mothers: Because of the potential for adverse reactions in nursing infants from TOBREX® (tobramycin ophthalmic ointment) 0.3%, a decision should be made whether to discontinue nursing the infant or discontinue the drug, taking into account the importance of the drug to the mother.

PEDIATRIC USE

Pediatric Use: Safety and effectiveness in pediatric patients below the age of 2 months has not been established.

GERIATRIC USE

Geriatric Use: No overall clinical differences in safety or effectiveness have been observed between the elderly and other adult patients.

ADVERSE REACTIONS

ADVERSE REACTIONS: The most frequent adverse reactions to TOBREX (tobramycin ophthalmic ointment) 0.3% are hypersensitivity and localized ocular toxicity, including lid itching and swelling, and conjunctival erythema. These reactions occur in less than three of 100 patients treated with TOBREX® (tobramycin ophthalmic ointment) 0.3%.

POSTMARKETING EXPERIENCE

Postmarketing Experience: Additional adverse reactions identified from postmarketing use include anaphylactic reaction, Stevens-Johnson syndrome, and erythema multiforme.

The following additional adverse reactions have been reported with systemic aminoglycosides:

Neurotoxicity, ototoxicity and nephrotoxicity have occurred in patients receiving systemic aminoglycoside therapy. Aminoglycosides may aggravate muscle weakness in patients with known or suspected neuromuscular disorders, such as myasthenia gravis or Parkinson’s disease, because of their potential effect on neuromuscular function.

DOSAGE AND ADMINISTRATION

In mild to moderate disease, apply a half-inch ribbon into the affected eye(s) 2 or 3 times per day. In severe infections, instill a half-inch ribbon into the affected eye(s) every 3 to 4 hours until improvement, following which treatment should be reduced prior to discontinuation.

How to Apply TOBREX (tobramycin ophthalmic ointment) 0.3%:

1. Tilt your head back.

2. Place a finger on your cheek just under your eye and gently pull down until a ''V'' pocket is formed between your eyeball and your lower lid.

3. Place a small amount (about ½ inch) of TOBREX® (tobramycin ophthalmic ointment) 0.3% in the ''V'' pocket. Do not let the tip of the tube touch your eye.

4. Look downward before closing your eye.

HOW SUPPLIED

TOBREX (tobramycin ophthalmic ointment) 0.3% is supplied as a 3.5 g sterile ointment in an aluminum tube with a white polyethylene tip and white polyethylene cap as follows:

3.5 g containing tobramycin 0.3% (3 mg/g).................................................. NDC 0078-0813-01

Storage: Store at 2°C to 25°C (36°F to 77°F).

After opening, TOBREX (tobramycin ophthalmic ointment) 0.3% can be used until the expiration date on the tube.

Distributed by:
Novartis Pharmaceuticals Corporation
East Hanover, New Jersey 07936

© Novartis

Revised: June 2021

T2021-76

PRINCIPAL DISPLAY PANEL

NDC 0078-0813-01

Tobrex®

(tobramycin ophthalmic
ointment) 0.3%

Sterile 3.5 g Net Wt.

NOVARTIS